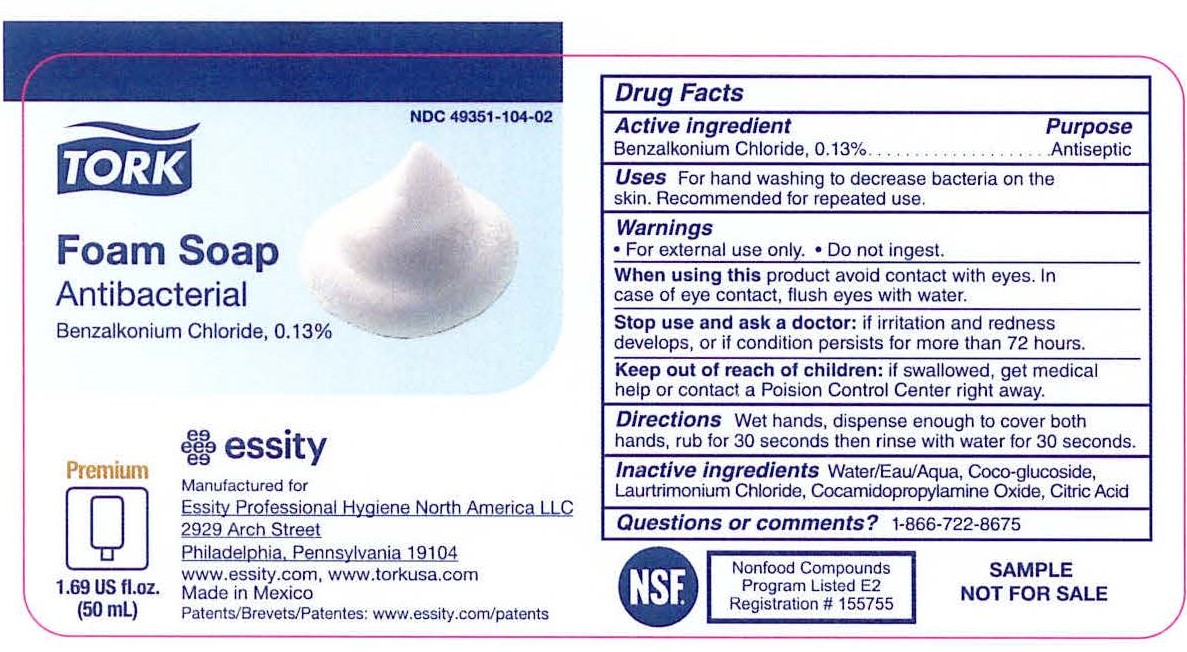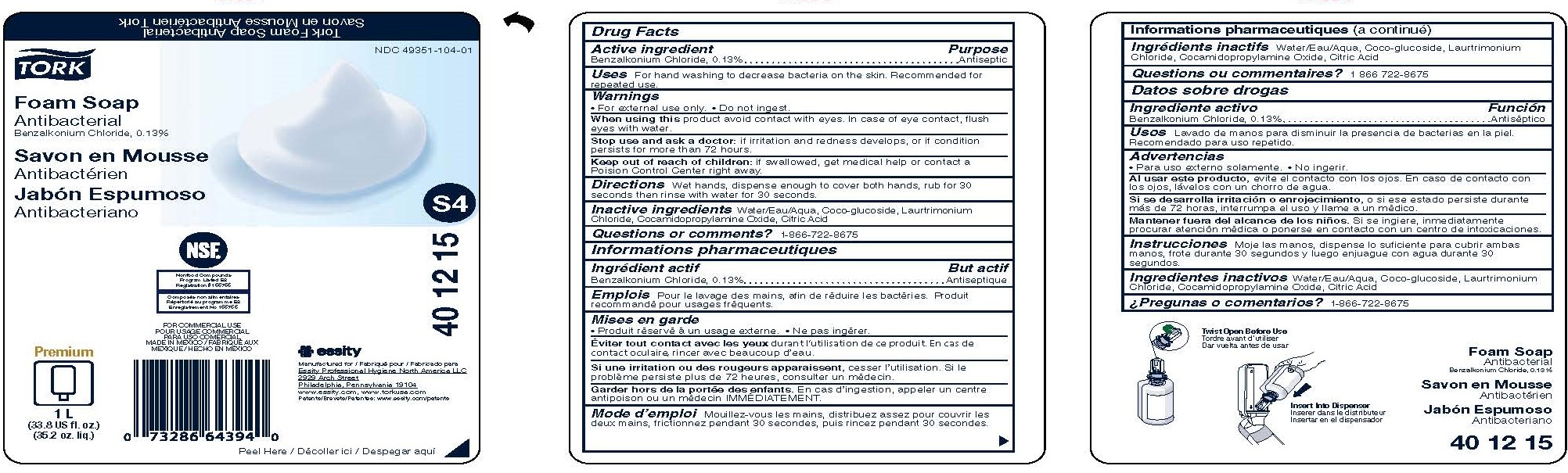 DRUG LABEL: Tork Foam Antibacterial
NDC: 49351-104 | Form: SOAP
Manufacturer: Essity Professional Hygiene North America LLC
Category: otc | Type: HUMAN OTC DRUG LABEL
Date: 20240502

ACTIVE INGREDIENTS: BENZALKONIUM CHLORIDE 0.13 g/100 mL
INACTIVE INGREDIENTS: COCO GLUCOSIDE; LAURTRIMONIUM CHLORIDE; WATER; COCAMIDOPROPYLAMINE OXIDE; ANHYDROUS CITRIC ACID

49351-104

Drug Facts

Active ingredient

Benzalkonium chloride, 0.13%

Purpose

Antiseptic

Uses

- For hand washing to decrease bacteria on the skin
- Recommended for repeated use

Warnings

For external use only

When using this

product avoid contact with eyes. In case of eye contact, flush eyes with water.

Stop use and ask a doctor if

irritation or redness develops, or if condition persists for more than 72 hours.

Keep out of reach of children.

If swallowed, get medical help or contact a Poison Control Center right away.

Directions

- Pump a small amount of foam into palm of hand
- Rub thoroughly over all surfaces of both hands for 15 seconds
- Rinse with potable water

Inactive ingredients

Water/Eau/Aqua, Coco-glucoside, Laurtrimonium Chloride, Cocamidopropylamine Oxide, Citric acid.

Questions or Comments?

1-866-722-8675

PACKAGE LABEL

TORK®

Foam Soap

Antibacterial

NDC 49351-104-01

Manufactured for Essity Professional Hygiene North America, LLC

2929 Arch Street

Philadelphia, PA 19104

www.torkusa.com

For Commercial use

Made in Mexico

Premium

1 L

(33.8 US fl. oz.)

(35.2 oz. liq.)